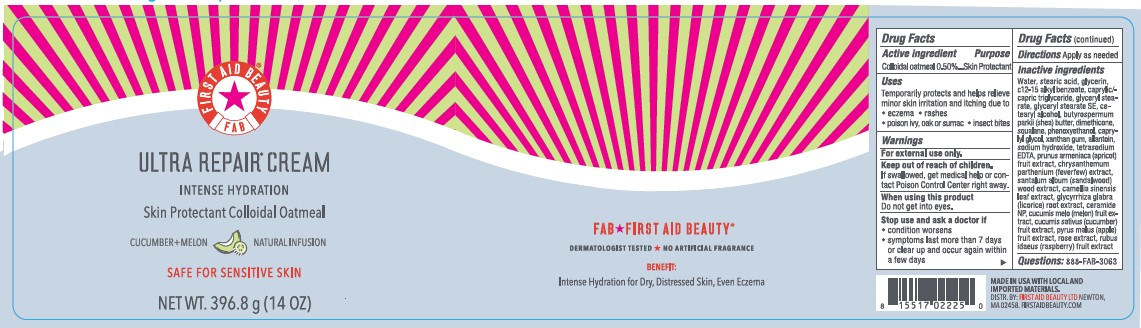 DRUG LABEL: First Aid Beauty FAB Ultra Repair Cream Intense Hydration Skin Protectant Cucumber Melon
NDC: 84126-102 | Form: CREAM
Manufacturer: The Procter & Gamble Manufacturing Company
Category: otc | Type: HUMAN OTC DRUG LABEL
Date: 20250307

ACTIVE INGREDIENTS: OATMEAL 0.5 g/100 g
INACTIVE INGREDIENTS: PYRUS MALUS (APPLE) FRUIT; SANTALUM ALBUM (SANDALWOOD); DIMETHICONE; PRUNUS ARMENIACA (APRICOT) FRUIT EXTRACT; CUCUMIS SATIVUS (CUCUMBER) FRUIT; RUBUS IDAEUS (RASPBERRY) FRUIT; MUSKMELON; SQUALANE; GLYCERYL STEARATE SE; CETEARYL ALCOHOL; TETRASODIUM EDTA; C12-15 ALKYL BENZOATE; SODIUM HYDROXIDE; PHENOXYETHANOL; BUTYROSPERMUM PARKII (SHEA) BUTTER; WATER; GLYCERIN; ALLANTOIN; GLYCERYL STEARATE; CAPRYLIC/CAPRIC TRIGLYCERIDE; STEARIC ACID; XANTHAN GUM; CERAMIDE NP; TANACETUM PARTHENIUM WHOLE; COCOS NUCIFERA (COCONUT) FRUIT; CAPRYLYL GLYCOL; GLYCYRRHIZA GLABRA (LICORICE) ROOT; CAMELLIA SINENSIS LEAF

First Aid Beauty FAB Ultra Repair Cream Skin Protectant Cucumber Melon

Drug Facts

Active ingredients

Colloidal Oatmeal 0.5%

Purpose

Skin Protectant

Uses

- Temporarily protects and helps relieve minor skin irritation and itching due to eczema, rashes, poison ivy, oak or sumac, insect bites

Warnings

For external use only.

Keep out of reach of children. If swallowed, get medical help or contact a Poison Control Center right away.

WHEN USING

Do not get into eyes.

Stop use and ask a doctor if condition worsens, symptoms last more than 7 days or clear up and occur again within a few days

Directions

Apply as needed

INACTIVE INGREDIENT

Water, stearic acid, glycerin, C12-15 alkyl benzoate, caprylic /capric triglyceride, glyceryl stearate, glyceryl stearate SE, cetearyl alcohol, butyrospermum parkii (shea) butter, dimethicone, squalane, phenoxyethanol, caprylyl glycol, xanthan gum, allantoin, sodium hydroxide, tetrasodium EDTA, prunus armeniaca (apricot) fruit extract, chrysanthemum parthenium (feverfew) extract, santalum album (sandalwood) wood extract, camellia sinensis leaf extract, glycyrrhiza glabra (licorice) root extract, ceramide NP, cucumis melo (melon) fruit extract, cucumis sativus (cucumber) fruit extract, pyrus malus (apple) fruit extract, rose extract, rubus idaeus (raspberry) fruit extract

Questions:

888-FAB-3063

MADE IN USA

FIRST AID BEAUTY LTD

NEWTON, MA 02458

WWW.FIRSTAIDBEAUTY.COM

PRINCIPAL DISPLAY PANEL - 396.8 g (14 oz)

First Aid Beauty

FAB

Ultra Repair® Cream

Intense Hydration

Skin Protectant Colloidal Oatmeal

CUCUMBER + MELON

Net Wt. 396.8 g (14 oz)